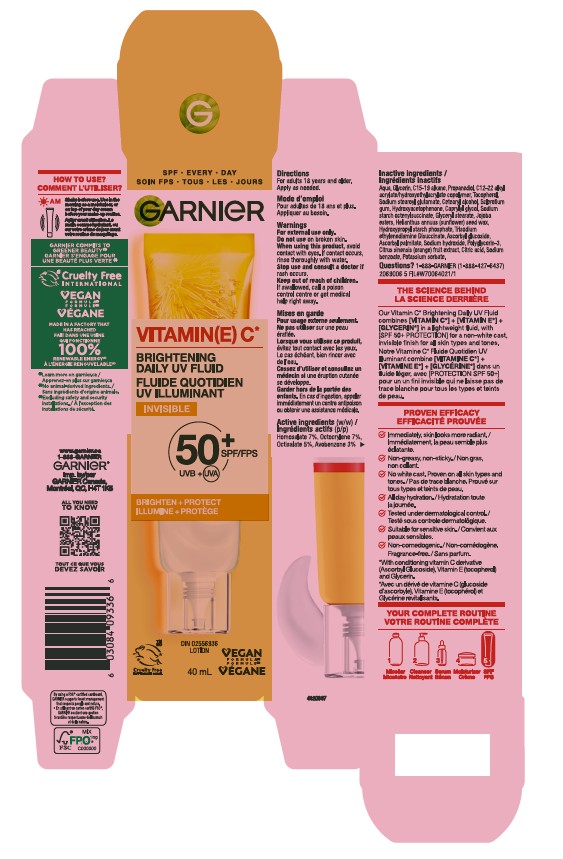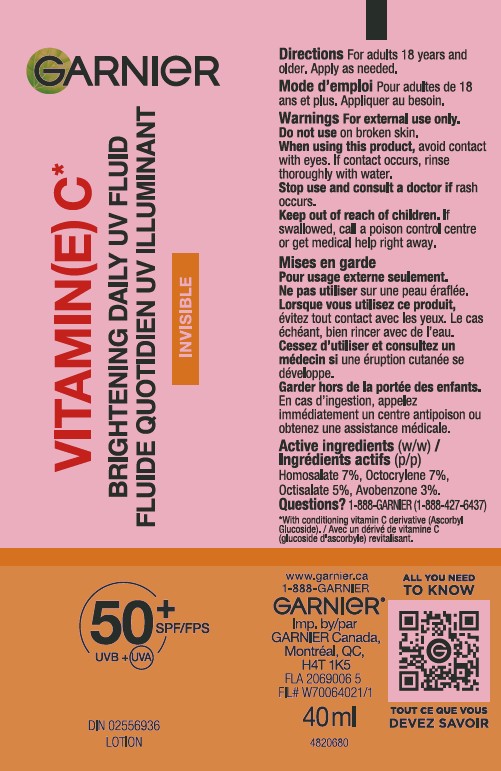 DRUG LABEL: Garnier VitaminE C Brightening Daily UV Fluid Invisible 50 plus SPF UVB plus UVA
NDC: 82046-336 | Form: LOTION
Manufacturer: L'Oreal USA Products Inc
Category: otc | Type: HUMAN OTC DRUG LABEL
Date: 20251209

ACTIVE INGREDIENTS: AVOBENZONE 30 mg/1 mL; OCTISALATE 50 mg/1 mL; OCTOCRYLENE 70 mg/1 mL; HOMOSALATE 70 mg/1 mL
INACTIVE INGREDIENTS: AQUA; GLYCERIN; C15-19 ALKANE; PROPANEDIOL; TOCOPHEROL; SODIUM STEAROYL GLUTAMATE; CETEARYL ALCOHOL; SCLEROTIUM GUM; HYDROXYACETOPHENONE; CAPRYLYL GLYCOL; GLYCERYL STEARATE; HELIANTHUS ANNUUS (SUNFLOWER) SEED WAX; HYDROXYPROPYL STARCH; TRISODIUM ETHYLENEDIAMINE DISUCCINATE; ASCORBYL GLUCOSIDE; ASCORBYL PALMITATE; SODIUM HYDROXIDE; Polyglycerin-3; CITRIC ACID; SODIUM BENZOATE; POTASSIUM SORBATE

Drug Facts

Directions

For adults 18 years and older. Apply as needed.

Warnings

For external use only.

Do not use

on broken skin.

When using this product,

avoid contact with eyes. If contact occurs, rinse thoroughly with water.

Stop use and consult a doctor

if rash occurs.

Keep out of reach of children.

If swallowed, call a poison control centre or get medical help right away.

Active ingredients

Homosalate 7%, Octocrylene 7%, Octisalate 5%, Avobenzone 3%

Inactive Ingredients

Aqua, Glycerin, C15-19 alkane, Propanediol, C12-22 alkyl acrylate/hydroxyethylacrylate copolymer, Tocopherol, Sodium stearoyl glutamate, Cetearyl alcohol, Sclerotium gum, Hydroxyacetophenone, Caprylyl glycol, Sodium starch octenylsuccinate, Glyceryl stearate, Jojoba esters, Helianthus annuus (sunflower) seed wax, Hydroxypropyl starch phosphate, Trisodium ethylenediamine Disuccinate, Ascorbyl glucoside, Ascorbyl palmitate, Sodium hydroxide, Polyglycerin-3, Citrus sinensis (orange) fruit extract, Citric acid, Sodium benzoate, Potassium sorbate

Questions?

1-888-GARNIER (1-888-427-6437)